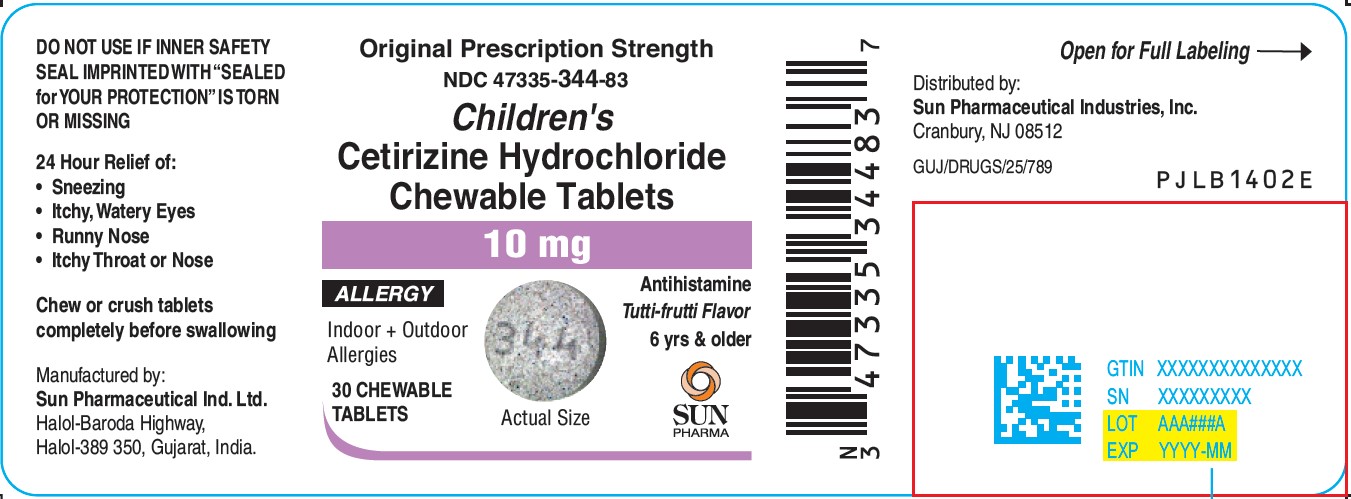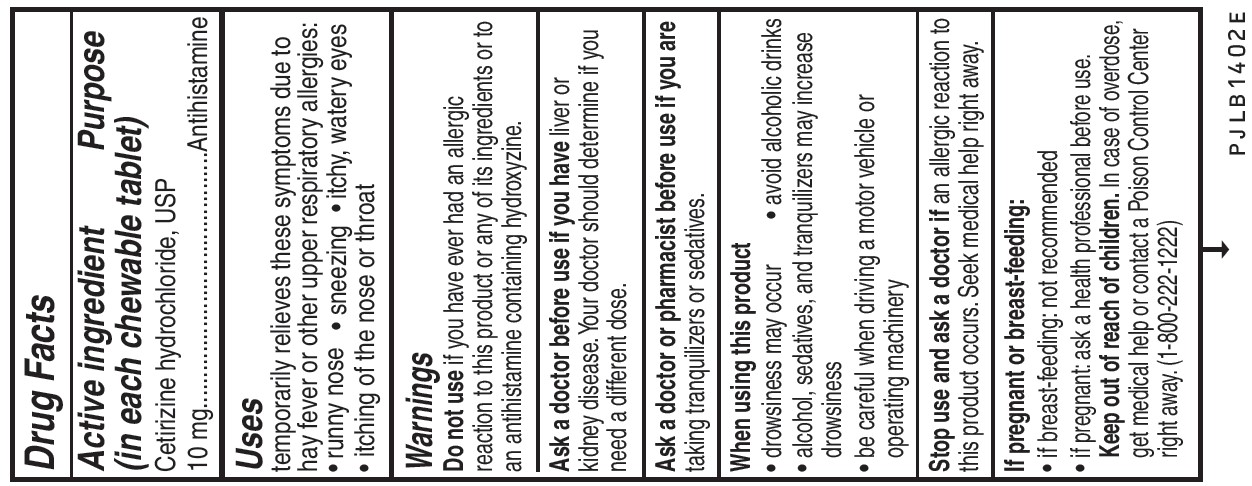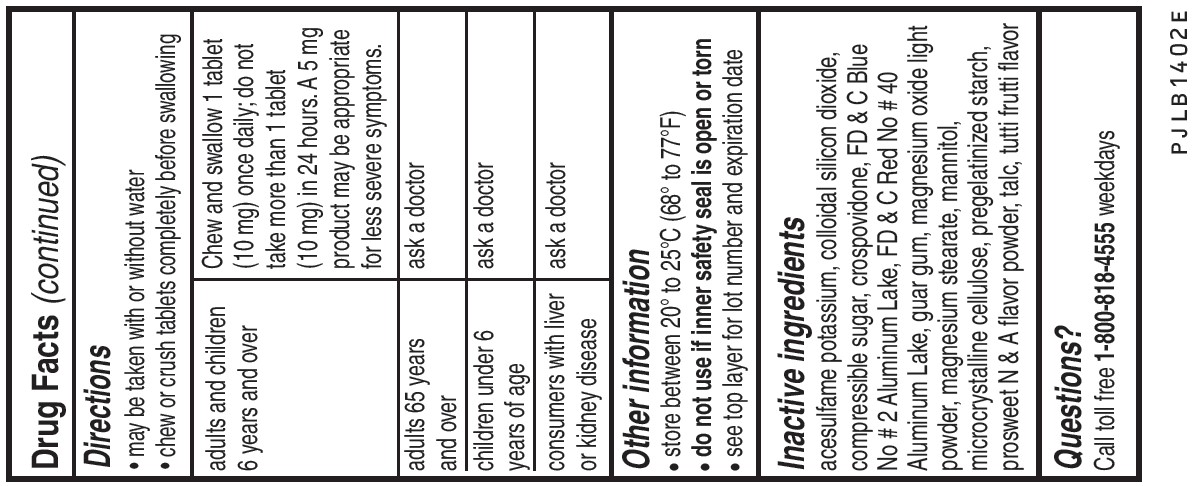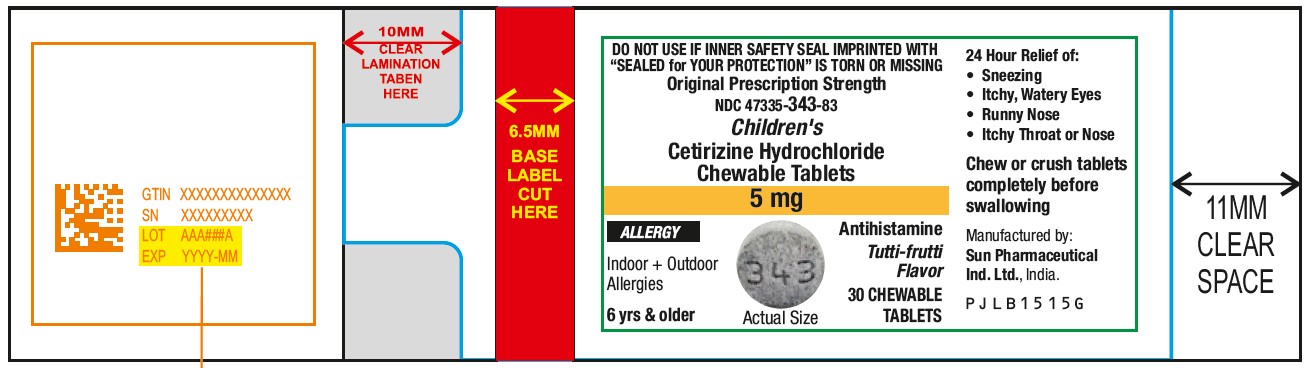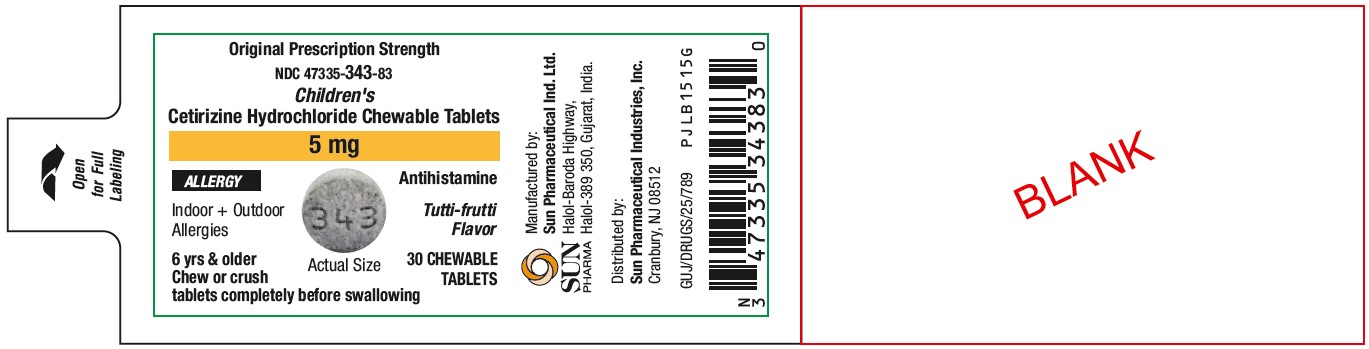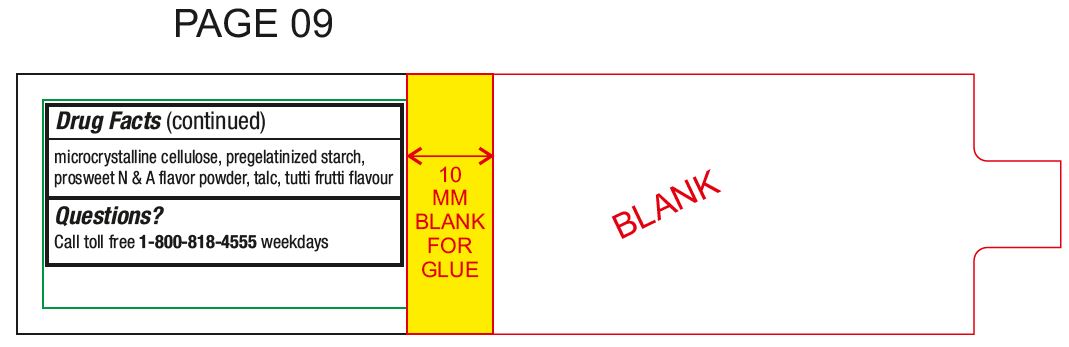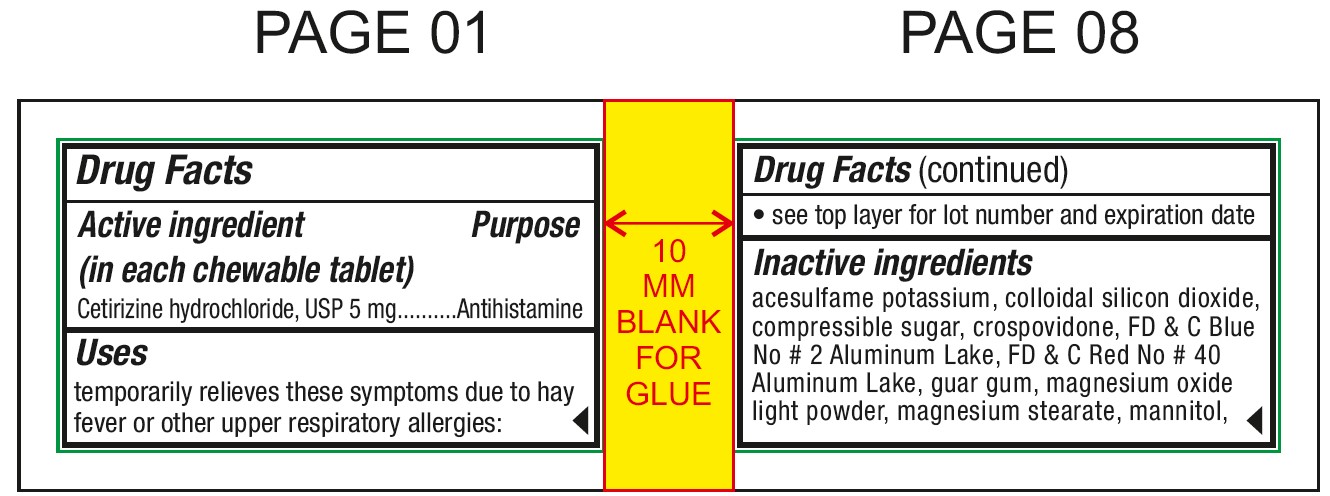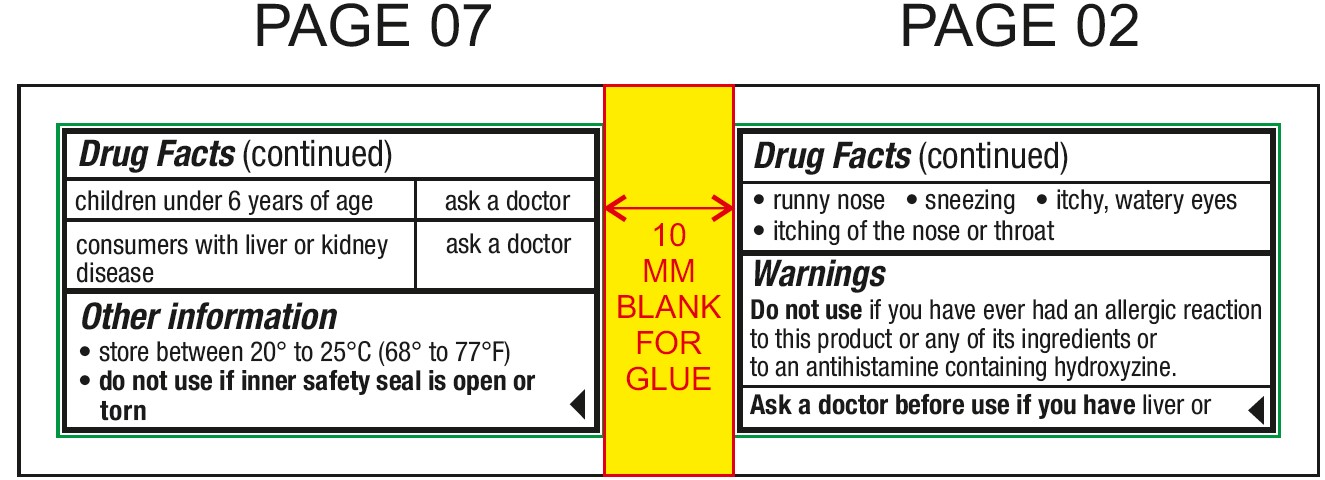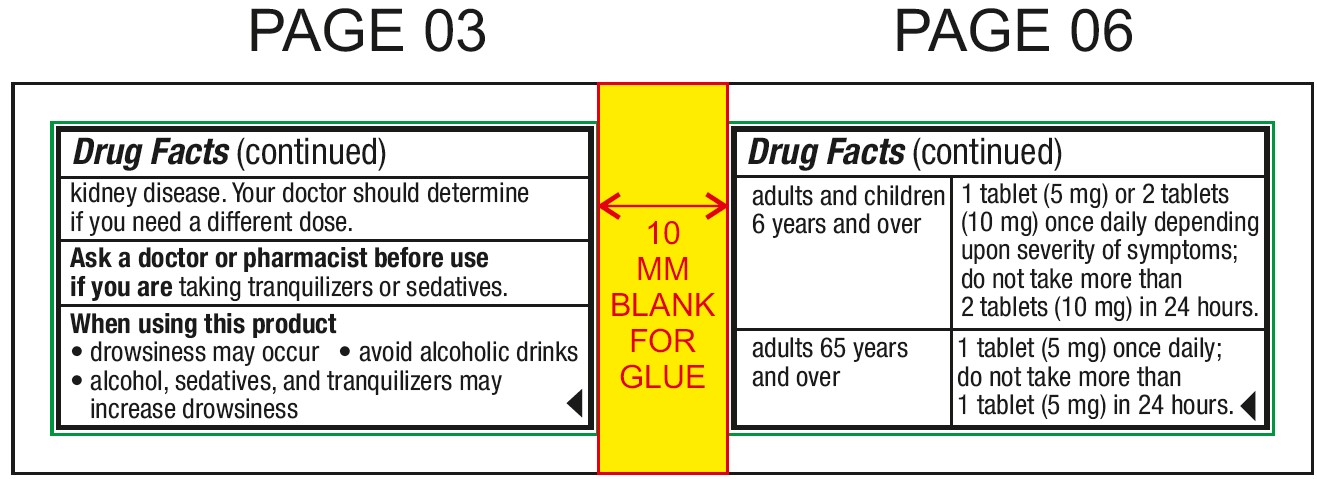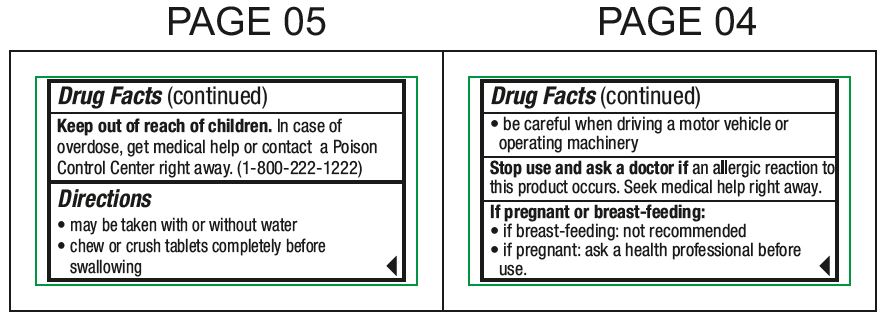 DRUG LABEL: Cetirizine Hydrochloride
NDC: 47335-343 | Form: TABLET, CHEWABLE
Manufacturer: Sun Pharmaceutical Industries, Inc.
Category: otc | Type: Human OTC Drug Label
Date: 20240916

ACTIVE INGREDIENTS: CETIRIZINE HYDROCHLORIDE 5 mg/1 1
INACTIVE INGREDIENTS: ACESULFAME POTASSIUM; SILICON DIOXIDE; SUCROSE; CROSPOVIDONE; FD&C BLUE NO. 2; FD&C RED NO. 40; GUAR GUM; MAGNESIUM OXIDE; MAGNESIUM STEARATE; MANNITOL; CELLULOSE, MICROCRYSTALLINE; STARCH, CORN; TALC

Cetirizine Hydrochloride Chewable Tablets

Active ingredient (in each chewable tablet)

For 5 mg:Cetirizine hydrochloride, USP 5 mg
For 10 mg:Cetirizine hydrochloride, USP 10 mg

Purpose

Antihistamine

Uses

temporarily relieves these symptoms due to hay fever or other upper respiratory allergies:

- runny nose
- sneezing
- itchy, watery eyes
- itching of the nose or throat

Do not use

if you have ever had an allergic reaction to this product or any of its ingredients or to an antihistamine containing hydroxyzine.

Ask a doctor before use if you have

liver or kidney disease. Your doctor should determine if you need a different dose.

Ask a doctor or pharmacist before use if

you are taking tranquilizers or sedatives.

When using this product

- drowsiness may occur
- avoid alcoholic drinks
- alcohol, sedatives, and tranquilizers may increase drowsiness
- be careful when driving a motor vehicle or operating machinery

Stop use and ask doctor if

an allergic reaction to this product occurs. Seek medical help right away.

If pregnant or breast-feeding:

- if breast-feeding: not recommended
- if pregnant: ask a health professional before use.

Keep out of reach of children

In case of overdose, get medical help or contact a Poison Control Center right away. (1-800-222-1222)

Directions

- may be taken with or without water
- chew or crush tablets completely before swallowing

For 5 mg:

adults and children 6 years and over | 1 tablet (5 mg) or 2 tablets (10 mg) once daily depending upon severity of symptoms; do not take more than 2 tablets (10mg) in 24 hours.
adults 65 years and over | 1 tablet (5 mg) once daily; do not take more than 1 tablet (5 mg) in 24 hours.
children under 6 years of age | ask a doctor
consumers with liver or kidney disease | ask a doctor

For 10 mg:

adults and children 6 years and over | Chew and swallow 1 tablet (10 mg) once daily; do not take more than 1 tablet (10 mg) in 24 hours. A 5 mg product may be appropriate for less severe symptoms.
adults 65 years and over | ask a doctor
children under 6 years of age | ask a doctor
consumers with liver or kidney disease | ask a doctor

Other information

- store between 20° to 25°C (68° to 77°F)
- do not use if inner safety seal is open or torn
- see top layer for lot number and expiration date

Inactive ingredients

acesulfame potassium, colloidal silicon dioxide, compressible sugar, crospovidone, FD & C Blue No # 2 Aluminum Lake, FD & C Red No # 40 Aluminum Lake, guar gum, magnesium oxide light powder, magnesium stearate, mannitol, microcrystalline cellulose, pregelatinized starch, prosweet N & A flavor powder, talc, tutti frutti flavor

Questions?

Call toll free 1-800-818-4555 weekdays

PACKAGE LABEL.PRINCIPAL DISPLAY PANEL

For 5 mg Allergy:
Original Prescription Strength
NDC 47335-343-83
Cetirizine Hydrochloride Chewable Tablets
5 mg
ALLERGY
Antihistamine
Indoor + Outdoor Allergies
Actual Size
Tutti-frutti Flavor
6 yrs & older
30 CHEWABLE TABLETS
SUN PHARMACEUTICAL INDUSTRIES LTD.

PACKAGE LABEL.PRINCIPAL DISPLAY PANEL

For 10 mg Allergy:
Original Prescription Strength
NDC 47335-344-83
Cetirizine Hydrochloride Chewable Tablets
10 mg
ALLERGY
Antihistamine
Indoor + Outdoor Allergies
Actual Size
Tutti-frutti Flavor
6 yrs & older
30 CHEWABLE TABLETS
SUN PHARMA